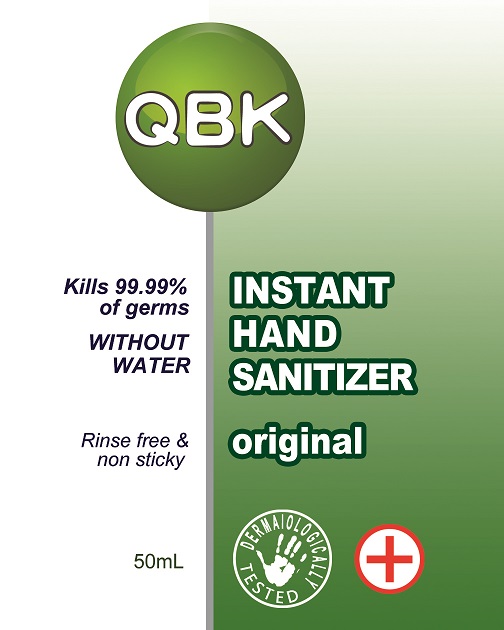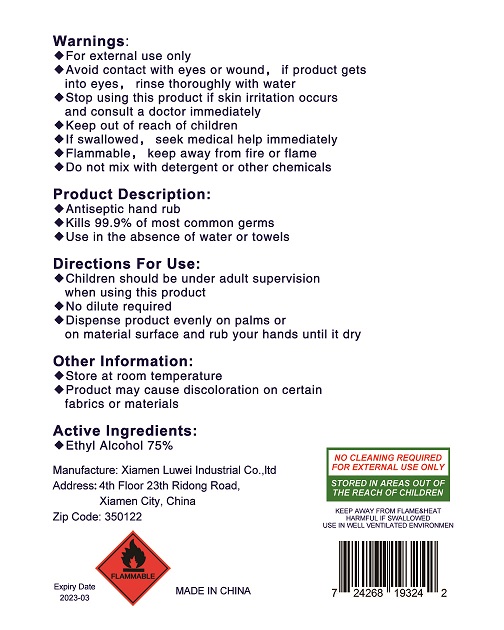 DRUG LABEL: Hand Sanitizer
NDC: 76846-1011 | Form: GEL
Manufacturer: Xiamen Luwei Industrial Co., Ltd
Category: otc | Type: HUMAN OTC DRUG LABEL
Date: 20200508

ACTIVE INGREDIENTS: ALCOHOL 37.5 mL/50 mL
INACTIVE INGREDIENTS: METHYL BENZOATE; CARBOMER INTERPOLYMER TYPE A (ALLYL SUCROSE CROSSLINKED); WATER; ALOE VERA LEAF; TROLAMINE

Luwei, Hand Sanitizer, Alcohol 75% v/v, Gel, 50mL

Active Ingredient(s)

Ethyl Alcohol 70% v/v. Purpose: Antimicrobial

Purpose

Antiseptic hand rub.

Use

Kills 99.9% of most common germs.
Use in the absence of water or towels.

Warnings

For external use only.

Flammable, keep away from fire or flame.

Do not mix with detergent or other chemicals.

Do not use

Avoid contact with eyes or wound, if product gets into eyes, rinse thoroughly with water.

When using this product, do not use in or near the eyes or wound.

Use in well ventilated environment.

STOP USE

Stop using this product if skin irritation occurs and consult a doctor immediately.

Keep out of reach of children.

If swallowed, seek medical help immediately.

Directions

- Dispense product evenly on palms or on material surface and rub your hands until dry.
- Children should be under adult supervision when using this product.
- No dilute required.

Other information

- Store at room temperature.
- Product may cause discoloration on certain fabrics or materials.

Inactive ingredients

Water, Carbomer, Triethanolamine, Aloe extract, Essence.